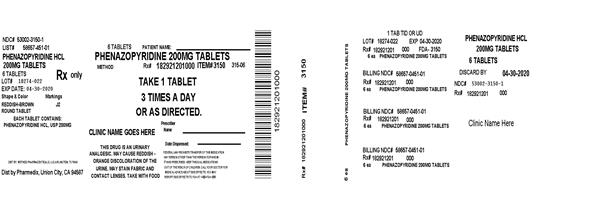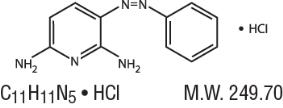 DRUG LABEL: Phenazopyridine HCl 200mg
NDC: 53002-3150 | Form: TABLET
Manufacturer: RPK Pharmaceuticals, Inc.
Category: prescription | Type: HUMAN PRESCRIPTION DRUG LABEL
Date: 20230607

ACTIVE INGREDIENTS: PHENAZOPYRIDINE HYDROCHLORIDE 200 mg/1 1
INACTIVE INGREDIENTS: SODIUM STARCH GLYCOLATE TYPE A CORN; MICROCRYSTALLINE CELLULOSE; MAGNESIUM STEARATE

Phenazopyridine HCl Oral Tablets, USP

Rx Only

DESCRIPTION

Phenazopyridine Hydrochloride is a reddish-brown, odorless, slightly bitter, crystalline powder. It has a specific local analgesic effect in the urinary tract, promptly relieving burning and pain.

Following is the structural formula:

Phenazopyridine HCl oral tablets contain the following inactive ingredients: Carnauba Wax, Croscarmellose Sodium, Hypromellose, Magnesium Stearate, Microcrystalline Cellulose, Polyethylene Glycol, Povidone, Pregelatinized Starch

CLINICAL PHARMACOLOGY

Phenazopyridine hydrochloride is excreted in the urine where it exerts a topical analgesic effect on the mucosa of the urinary tract. This action helps to relieve pain, burning, urgency and frequency. The precise mechanism of action is unknown.

PHARMACOKINETICS

The pharmacokinetic properties of phenazopyridine hydrochloride have not been determined. Phenazopyridine and its metabolites are rapidly excreted by the kidneys. In a small number of healthy subjects, 90% of a 600 mg/day oral dose of phenazopyridine hydrochloride was eliminated in the urine in 24 hours, 41% as unchanged drug and 49% as metabolites.

INDICATIONS AND USAGE

Phenazopyridine HCl is indicated for the symptomatic relief of pain, burning, urgency frequency, and other discomforts arising from irritation of the mucosa of the lower urinary tract caused by infection, trauma, surgery, endoscopic procedures, or the passage of sounds or catheters.

The use of phenazopyridine for relief of symptoms should not delay definitive diagnosis and treatment of causative conditions. The drug should be used for symptomatic relief of pain and not as a substitute for specific surgery or antimicrobial therapy.

Phenazopyridine is compatible with antimicrobial therapy and can help relieve pain and discomfort during the interval before antimicrobial therapy controls the infection.

Treatment of a urinary tract infection with phenazopyridine should not exceed 2 days. There is no evidence that the combined administration of phenazopyridine and an antimicrobial provides greater benefit than administration of the antimicrobial alone after 2 days. (See Dosage and Administration.)

CONTRAINDICATIONS

In patients who are hypersensitive to the drug or its ingredients. Phenazopyridine is contraindicated in patients with renal insufficiency, severe liver disease, severe hepatitis or pyelonephritis of pregnancy.

It should be used cautiously in the presence of GI disturbances.

WARNINGS

Phenazopyridine hydrochloride is reasonably anticipated to be a human carcinogen based on sufficient evidence of carcinogenicity in experimental animals (IARC 1980, 1982, 1987, NCI 1978). When administered in the diet, phenazopyridine hydrochloride increased the incidences of hepatocellular adenomas and carcinomas in female mice and adenomas and adenocarcinomas of the colon and rectum in rats of both sexes.

There is inadequate evidence for the carcinogenicity of phenazopyridine hydrochloride in humans (IARC 1987). In one limited epidemiological study, no significant excess of any cancer was observed among 2,214 patients who received phenazopyridine hydrochloride and were followed for a minimum of 3 years.

PRECAUTIONS

General:

The patient should be advised that phenazopyridine produces an orange to red color in the urine and feces, and may cause staining. Phenazopyridine may cause discoloration of body fluids and staining of contact lenses has been reported. A yellowish color of the skin or sclera may indicate accumulation of phenazopyridine resulting from impaired renal function and necessitates discontinuance of the drug. It should be noted that a decline in renal function is common in elderly patients. Phenazopyridine may mask pathological conditions and interfere with laboratory test values using colorimetric, spectrophotometric or fluorometric analysis methods.

Cautious use in patients with G-6-PD deficiency is advised since these patients are susceptible to oxidative hemolysis and may have greater potential to develop hemolytic anemia.

Information for Patients:

The patient should be advised to take phenazopyridine with or following food or after eating a snack to reduce stomach upset.

The patients should be aware that phenazopyridine causes a reddish orange discoloration of the urine and feces, and may stain clothing. Phenazopyridine may cause discoloration of body fluids and staining of contact lenses has been reported. There have been reports of teeth discoloration when the product has been broken or held in the mouth prior to swallowing.

Patients should be instructed to take phenazopyridine for only 2 days if an antibacterial agent is administered concurrently for the treatment of a urinary tract infection. If symptoms persist beyond those 2 days, the patient should be instructed to contact his or her physician.

Laboratory Tests:

Phenazopyridine may interfere with laboratory test values using colorimetric, photometric or fluorometric analysis methods.

Altered urine laboratory test values may include ketone (sodium nitroprusside), bilirubin (foam test, talc-disk-Fouchet-spot test, Franklin's tablet-Fouchet test, p-nitrobenzene diazonium p-toluene sulfonate reagent), diacetic acid (Gerhardt ferric chloride test), free hydrochloric acid, glucose (glucose oxidase tests), 17-hydroxycorticosteroids (modified Glenn-Nelson), 17-ketosteroids (Holtorff Koch modification of Zimmerman), porphyrins, albumin (discolors bromophenol blue test areas of commercial reagent strips, nitric acid ring test), phenolsulfophthalein, urobilinogen (color interference with Ehrlich's reagent), and urinalysis (spectrophotometric or color-based tests). Phenazopyridine also imparts an orange-red color to stools which may interfere with color tests.

Drug Interactions:

The interaction of phenazopyridine with other drugs has not been studied in a systematic manner. However, the medical literature to date suggests that no significant interactions have been reported.

Carcinogenesis, Mutagenesis, Impairment of Fertility:

Long-term administration of phenazopyridine has been associated with tumors of the large intestine in rats and of the liver in mice. Available epidemiological data are insufficient to evaluate the carcinogenicity of phenazopyridine in humans. In vitro studies indicate that phenazopyridine in the presence of metabolic activation is mutagenic in bacteria and mutagenic and clastogenic in mammalian cells.

Pregnancy Category B:

Reproductive studies with phenazopyridine (in combination with sulfacytine) in rats given up to 110 mg/kg/day and in rabbits given up to 39 mg/kg/day during organogenesis revealed no evidence of harm to offspring.

One prospective study in humans demonstrated that phenazopyridine traverses the placenta into the fetal compartment. There are no adequate and well-controlled studies in pregnant women. Therefore, phenazopyridine should be used in pregnant women only if the benefit clearly outweighs the risk.

Nursing Mothers:

It is not known whether phenazopyridine or its metabolites are excreted in human milk. Because many drugs are excreted in human milk, a decision should be made to discontinue nursing or to discontinue the drug, taking into account the importance of drug therapy to the mother.

Children:

Adequate and well-controlled studies have not been performed in the pediatric population. No pediatric-specific problems have been documented.

ADVERSE REACTIONS

The following adverse events have been reported:

CNS: headache.

Gastrointestinal: nausea, vomiting and diarrhea.

Dermatologic and Hypersensitivity: rash, pruritus, discoloration, anaphylactoid-like reaction and hypersensitivity hepatitis

Hematologic: methemoglobinemia, hemolytic anemia, potential hemolytic agent in G-6-PD deficiency, sulfhemoglobinemia.

Other: visual disturbances, renal and hepatic toxicity usually associated with overdose, renal calculi, jaundice, discoloration of body fluids and aseptic meningitis.

OVERDOSAGE

Symptoms: Exceeding the recommended dose in patients with normal renal function or administering the recommended dose to patients with impaired renal function (common in elderly patients) may lead to increased serum levels and toxic reactions. Methemoglobinemia generally follows a massive, acute overdose. Methylene blue, 1 to 2 mg/kg/dose given i.v. as a 1% solution as needed, should cause prompt reduction of the methemoglobinemia and disappearance of the cyanosis which is an aid in diagnosis. Oxidative Heinz body hemolytic anemia also may occur, and "bite cells" (degmacytes) may be present in a chronic overdosage situation. Red blood cell G-6-PD deficiency may predispose to hemolysis; however, hemolysis may occur at normal doses in patients with G-6-PD Mediterranean.

Renal toxicity and occasional failure and hepatic impairment may also occur.

Treatment: Treatment is symptomatic and supportive.

DOSAGE AND ADMINISTRATION

Adults: 200 mg 3 times daily after meals. When used concomitantly with an antibacterial agent for the treatment of a urinary tract infection, the administration of phenazopyridine should not exceed 2 days. If symptoms persist, the patient should be re-evaluated.

HOW SUPPLIED

Product: 53002-3150

NDC: 53002-3150-1 6 TABLET in a BOTTLE

NDC: 53002-3150-2 9 TABLET in a BOTTLE